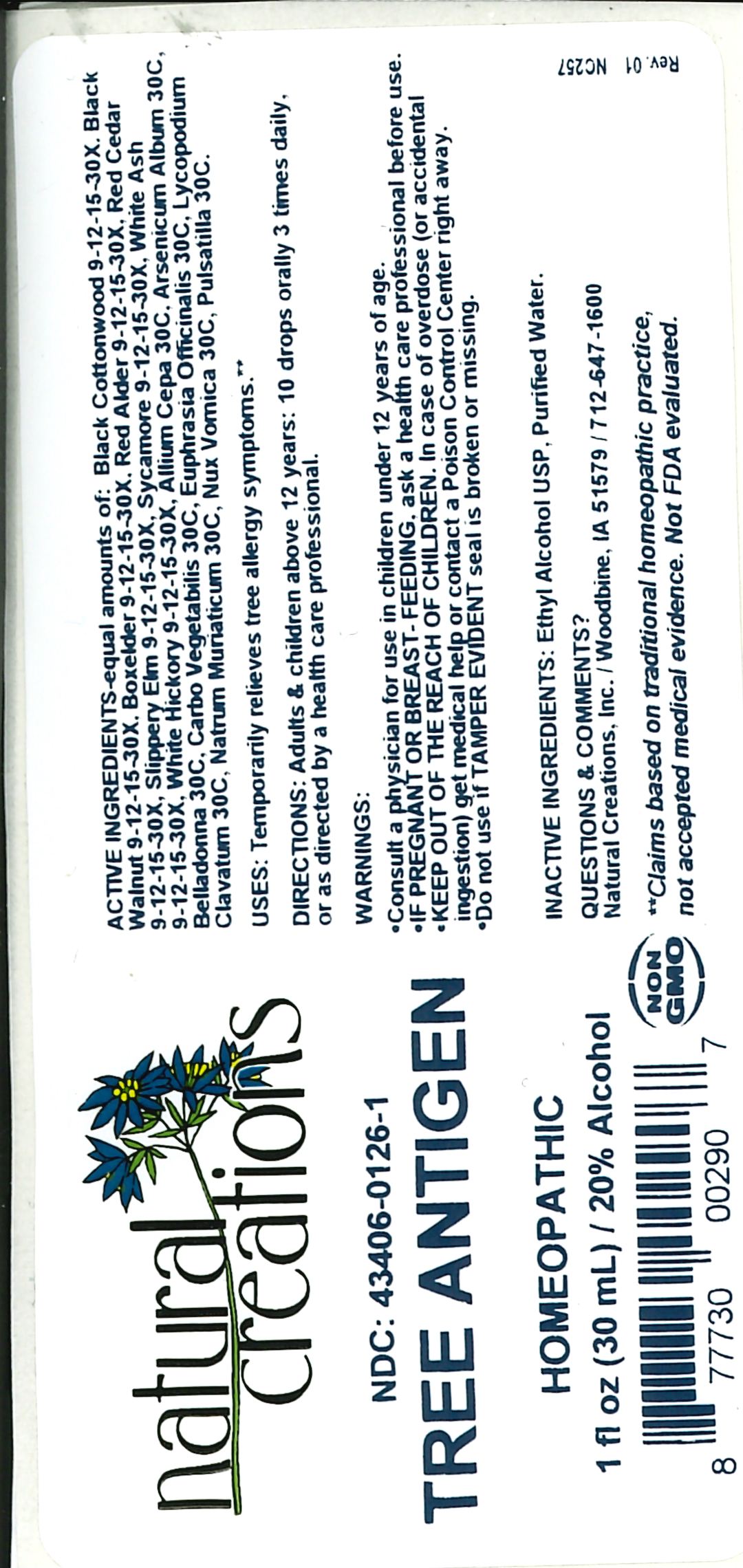 DRUG LABEL: TREE ANTIGEN
NDC: 43406-0126 | Form: LIQUID
Manufacturer: Natural Creations, Inc
Category: homeopathic | Type: HUMAN OTC DRUG LABEL
Date: 20241223

ACTIVE INGREDIENTS: POPULUS TRISTIS POLLEN 30 [hp_X]/1 mL; JUGLANS NIGRA POLLEN 30 [hp_X]/1 mL; ACER NEGUNDO POLLEN 30 [hp_X]/1 mL; ALNUS RUBRA POLLEN 30 [hp_X]/1 mL; JUNIPERUS VIRGINIANA POLLEN 30 [hp_X]/1 mL; ULMUS RUBRA POLLEN 30 [hp_X]/1 mL; ACER PSEUDOPLATANUS POLLEN 30 [hp_X]/1 mL; FRAXINUS AMERICANA POLLEN 30 [hp_X]/1 mL; CARYA TOMENTOSA POLLEN 30 [hp_X]/1 mL; ONION 30 [hp_C]/1 mL; ARSENIC TRIOXIDE 30 [hp_C]/1 mL; ATROPA BELLADONNA 30 [hp_C]/1 mL; ACTIVATED CHARCOAL 30 [hp_C]/1 mL; EUPHRASIA OFFICINALIS LEAF 30 [hp_C]/1 mL; LYCOPODIUM CLAVATUM SPORE 30 [hp_C]/1 mL; SODIUM CHLORIDE 30 [hp_C]/1 mL; STRYCHNOS NUX-VOMICA SEED 30 [hp_C]/1 mL; Pulsatilla Vulgaris 30 [hp_C]/1 mL
INACTIVE INGREDIENTS: ALCOHOL; WATER

TREE ANTIGEN

ACTIVE INGREDIENT

ACTIVE INGREDIENTS-equal amounts of: Black Cottonwood 9-12-15-30X, Black Walnut 9-12-15-30X, Boxelder 9-12-15-30X, Red Alder 9-12-15-30X, Red Cedar 9-12-15-30X, Slippery Elm 9-12-15-30X, Sycamore 9-12-15-30X, White Ash 9-12-15-30X, White Hickory 9-12-15-30X, Allium Cepa 30C, Arsenicum Album 30C, Belladonna 30C, Carbo Vegetabilis 30C, Euphrasia Officinalis 30C, Lycopodium Clavatum 30C, Natrum Muriaticum 30C, Nux Vomica 30C, Pulsitilla 30C.

INDICATIONS AND USAGE

USES: Temporarily relieves tree allegy symptoms.**

PURPOSE

Temporarily relieves tree allergy symptoms.**

DOSAGE AND ADMINISTRATION

DIRECTIONS: Adults & children above 12 years: 10 drops orally 3 times daily, or as directed by a health care professional.

KEEP OUT OF REACH OF CHILDREN

KEEP OUT OF THE REACH OF CHILDREN. In case of overdose (or accidental ingestion) get medical help or contact a Poison Control Center right away.

WARNINGS:

- Consult a physician for use in children under 12 years of age.
- IF PREGNANT OR BREAST-FEEDING, ask a health care professional before use.
- KEEP OUT OF THE REACH OF CHILDREN. In case of overdose (or accidental ingestion) get medical help or contact a Poison Control Center right away.
- Do not use if TAMPER EVIDENT seal is broken or missing.

INACTIVE INGREDIENTS: Ethyl Alcohol USP, Purified Water

QUESTIONS & COMMENTS?

Natural Creations, Inc. / Woodbine, IA 51579 / 712-647-1600

REFERENCES

**Claims based on traditional homeopathic practice, not accepted medical evidence. Not FDA evaluated.

PACKAGE LABEL

NDC:43406-0126-1

TREE ANTIGEN

HOMEOPATHIC

1 fl oz (30mL) /20% Alcohol